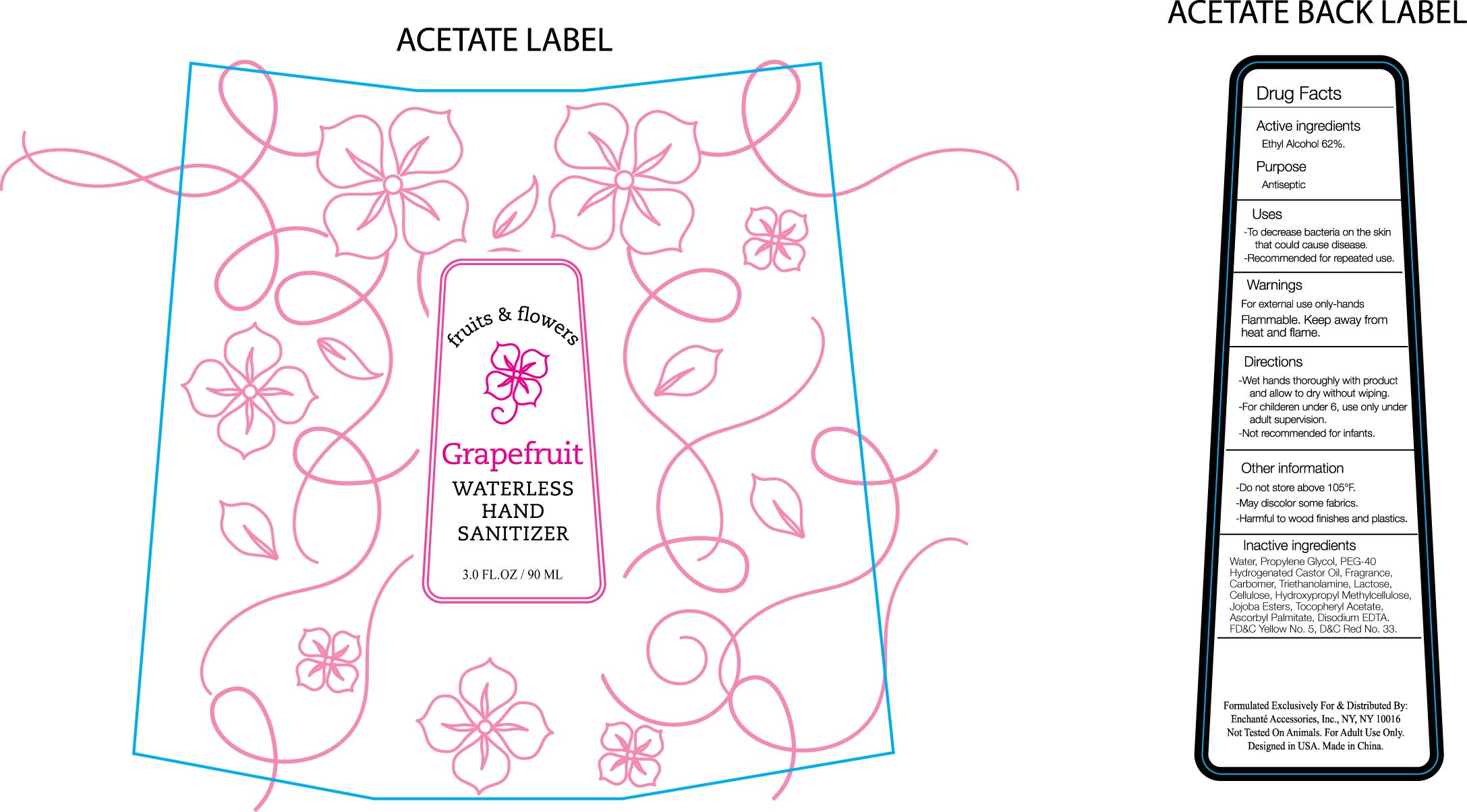 DRUG LABEL: Friuts and Flowers Grapefruit Waterless Hand Sanitizer
NDC: 49981-023 | Form: LIQUID
Manufacturer: Xiamen Anna Global Co., Ltd
Category: otc | Type: HUMAN OTC DRUG LABEL
Date: 20100806

ACTIVE INGREDIENTS: ALCOHOL 62.00 g/100 g
INACTIVE INGREDIENTS: WATER 34.049925 g/100 g; PROPYLENE GLYCOL 1.8 g/100 g; POLYOXYL 40 HYDROGENATED CASTOR OIL 1.0 g/100 g; CARBOMER COPOLYMER TYPE A 0.29 g/100 g; TROLAMINE 0.28 g/100 g; ANHYDROUS LACTOSE 0.01 g/100 g; CELLULOSE, MICROCRYSTALLINE 0.01 g/100 g; EDETATE DISODIUM 0.03 g/100 g; D&C RED NO. 33 0.0000625 g/100 g; FD&C YELLOW NO. 5 0.0000125 g/100 g; HYPROMELLOSE 2208 (15000 CPS) 0.01 g/100 g; ALPHA-TOCOPHEROL ACETATE 0.01 g/100 g; ASCORBYL PALMITATE 0.01 g/100 g; GRAPEFRUIT 0.5 g/100 g

Drug Fact

Active ingredients

Ethyl Alcohol 62%

Purpose:
Antiseptic

.

Uses
To decrease bacteria on hands that can cause disease
Recommended for repeated use.

Warnings
For external use only
Flammable: Keep away from heat and flame
Other Information:
Do not store above 105F
May discolor some fabrics
Harmful to wood finishes and plastics

Directions
Wet hands thoroughly with products and allow to dry without wiping.

For children under 6, use under adult supervision

Not recommended for infants.

Inactive Ingredients
Water, Propylene Glycol, PEG-40 Hydrogenated Castor Oil, Fragrance, Carbomer, Triethanolamine, Lactose, Cellulose, Hydroxypropyl Methylcellulose, Jojoba Ester, Tocopheryl Acetate, Ascorbyl Palmitate, Disodium EDTA, D and C red No. 33, FD and C Yellow No. 5

label